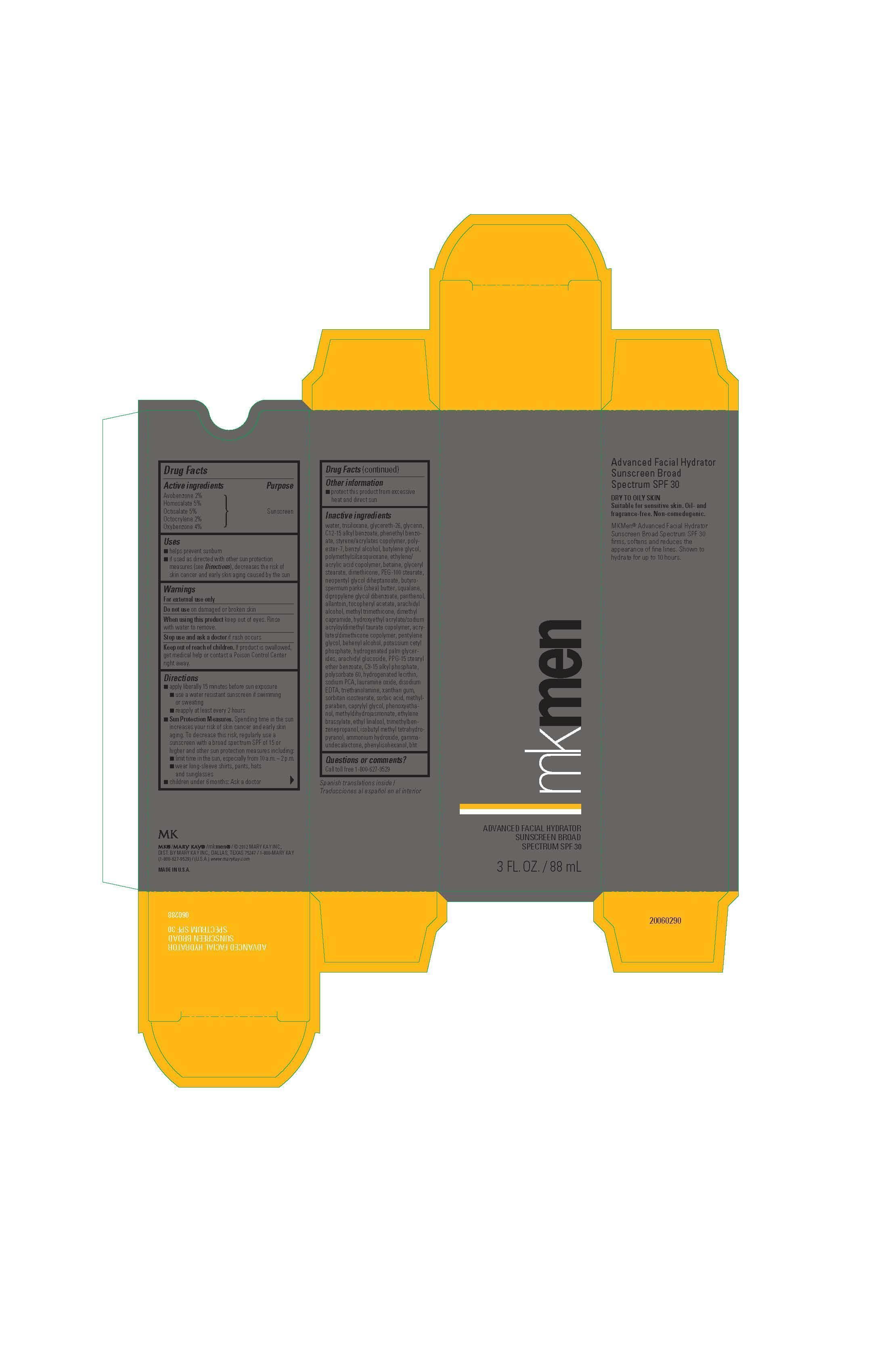 DRUG LABEL: MKMen Advanced Facial Hydrator Sunscreen SPF 30
NDC: 51531-0288 | Form: LOTION
Manufacturer: Mary Kay Inc.
Category: otc | Type: HUMAN OTC DRUG LABEL
Date: 20241219

ACTIVE INGREDIENTS: AVOBENZONE 2 g/100 mL; HOMOSALATE 5 g/100 mL; OCTISALATE 5 g/100 mL; OCTOCRYLENE 2 g/100 mL; OXYBENZONE 4 g/100 mL
INACTIVE INGREDIENTS: WATER; TRISILOXANE; GLYCERETH-26; GLYCERIN; ALKYL (C12-15) BENZOATE; PHENETHYL BENZOATE; POLYESTER-7; BENZYL ALCOHOL; BETAINE; BUTYLENE GLYCOL; POLYMETHYLSILSESQUIOXANE (4.5 MICRONS); ACRYLIC ACID/ETHYLENE COPOLYMER (600 MPA.S); GLYCERYL MONOSTEARATE; DIMETHICONE; PEG-100 STEARATE; NEOPENTYL GLYCOL DIHEPTANOATE; PHENOXYETHANOL; HYDROXYETHYL ACRYLATE/SODIUM ACRYLOYLDIMETHYL TAURATE COPOLYMER (45000 MPA.S AT 1%); DIPROPYLENE GLYCOL DIBENZOATE; CAPRYLYL GLYCOL; ARACHIDYL ALCOHOL; METHYL TRIMETHICONE; DIMETHYL CAPRAMIDE; SQUALANE; SHEA BUTTER; PENTYLENE GLYCOL; DOCOSANOL; POTASSIUM CETYL PHOSPHATE; XANTHAN GUM; LAURAMINE OXIDE; EDETATE DISODIUM; HYDROGENATED PALM GLYCERIDES; METHYLPARABEN; ARACHIDYL GLUCOSIDE; PPG-15 STEARYL ETHER BENZOATE; POLYSORBATE 60; .ALPHA.-TOCOPHEROL ACETATE; PANTHENOL; HYDROGENATED SOYBEAN LECITHIN; SORBIC ACID; ALLANTOIN; METHYL DIHYDROJASMONATE (SYNTHETIC); SODIUM PYRROLIDONE CARBOXYLATE; TROLAMINE; BUTYLATED HYDROXYTOLUENE; SORBITAN ISOSTEARATE; ETHYLENE BRASSYLATE; ETHYL LINALOOL; TRIMETHYLBENZENEPROPANOL; 2-ISOBUTYL-4-METHYLTETRAHYDROPYRAN-4-OL; AMMONIA; .GAMMA.-UNDECALACTONE; PHENYLISOHEXANOL

MKMen Advanced Facial Hydrator SPF 30
Drug Facts

Active Ingredients

Avobenzone 2%

Homosalate 5%

Octisalate 5%

Octocrylene 2%

Oxybenzone 4%

Purpose

Sunscreen

Uses

- helps prevent sunburn
- if used as directed with other sun protection measures (see Directions), decreases the risk of skin cancer and early skin aging caused by the sun

Warnings

For external use only

Do not use

on damaged or broken skin

When using this product

keep out of eyes. Rinse with water to remove.

Stop use and ask a doctor

if rash occurs

Keep out of reach of children.

If product is swallowed, get medical help or contact a Poison Control Center right away.

Directions

- apply liberally 15 minutes before sun exposure
- use a water resistant sunscreen if swimming or sweating
- reapply at least every 2 hours
- Sun Protection Measures. Spending time in the sun increases your risk of skin cancer and early skin aging. To decrease this risk, regularly use a sunscreen with a broad spectrum SPF of 15 or higher and other sun protection measures including:
- limit time in the sun, especially from 10 a.m. - 2 p.m.
- wear long-sleeve shirts, pants, hats, and sunglasses
- children under 6 months: Ask a doctor

Inactive ingredients

water, glycereth-26, dimethicone, glycerin, C12-15 alkyl benzoate, phenethyl benzoate, styrene/acrylates copolymer, trisiloxane, polyester-7, benzyl alcohol, butylene glycol, polymethylsilsesquioxane, ethylene/acrylic acid copolymer, betaine, glyceryl stearate, dimethicone, PEG-100 stearate, neopentyl glycol diheptanoate, butyrospermum parkii (shea) butter, squalane, dipropylene glycol dibenzoate, panthenol, allantoin, tocopheryl acetate, arachidyl alcohol, methyl trimethicone, dimethyl capramide, hydroxyethyl acrylate/sodium acryloyldimethyl taurate copolymer, acrylates/dimethicone copolymer, pentylene glycol, behenyl alcohol, potassium cetyl phosphate, hydrogenated palm glycerides, arachidyl glucoside, PPG-15 stearyl ether benzoate, C9-15 alkyl phosphate, polysorbate 60, hydrogenated lecithin, sodium PCA, lauramine oxide, disodium EDTA, triethanolamine, xanthan gum, sorbitan isostearate, sorbic acid, methylparaben, caprylyl glycol, phenoxyethanol, methyldihydrojasmonate, ethylene brassylate, ethyl linalool, trimethylbenzenepropanol, isobutyl methyl tetrahydropyranol, ammonium hydroxide, gamma-undecalactone, phenylisohexanol, BHT

Other information

- protect this product from excessive heat and direct sun

Questions or comments?

Call toll free 1-800-627-9529

Principal Display Panel - 88 mL carton

mkmen

Advanced Facial Hydrator

Sunscreen Broad Spectrum SPF 30

3 FL. OZ. / 88 mL